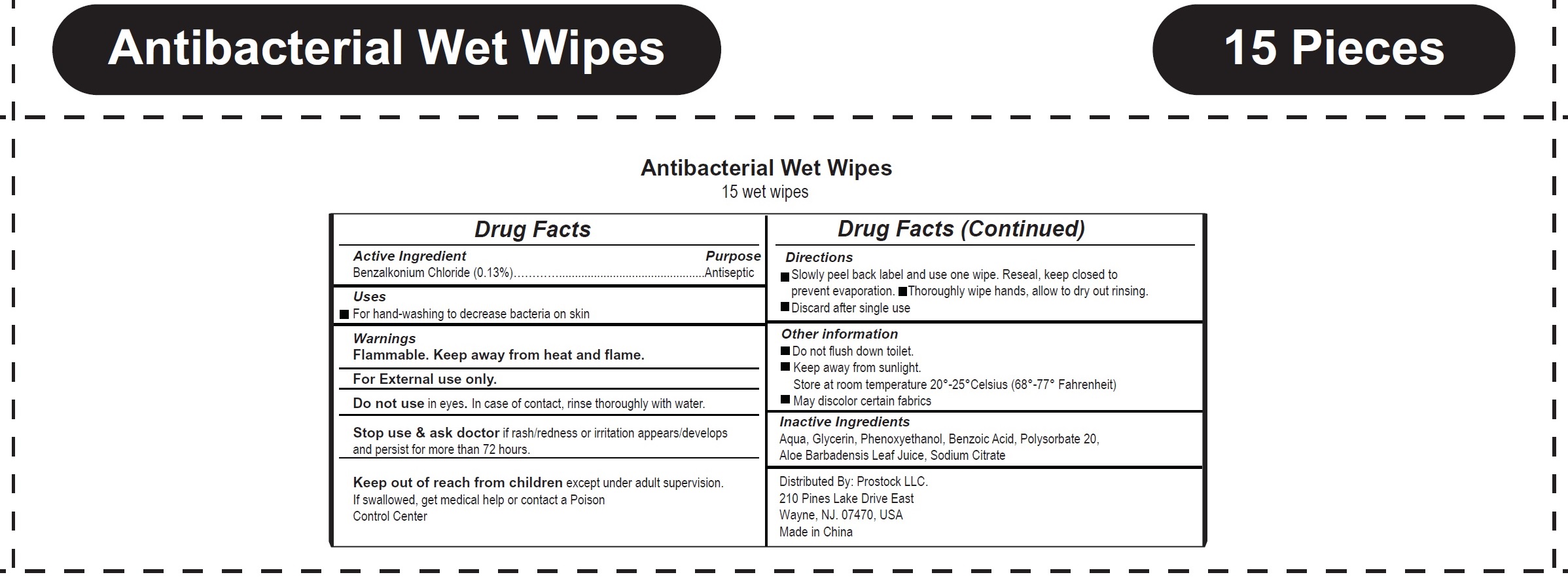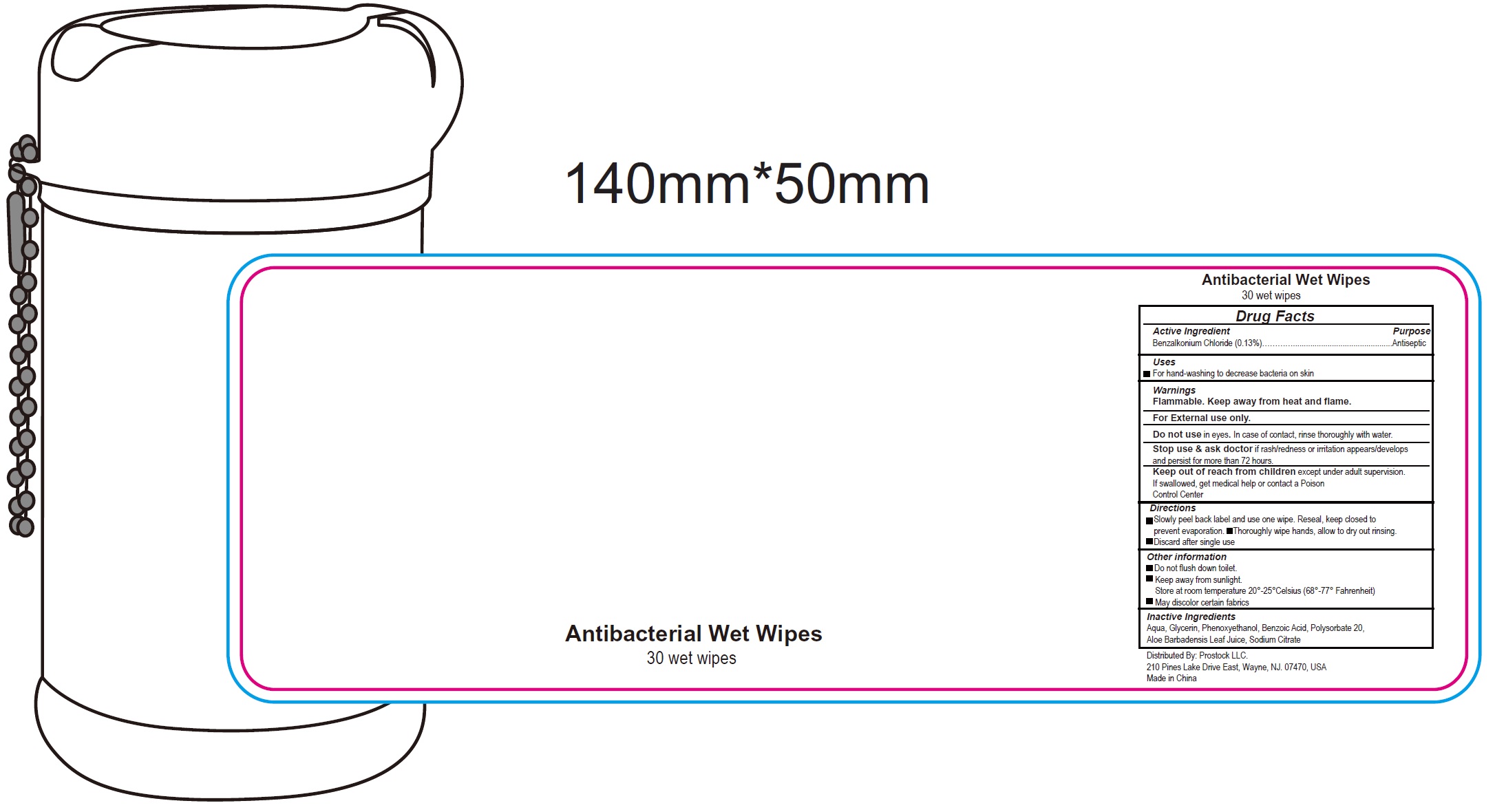 DRUG LABEL: Antibacterial Wet Wipes
NDC: 73796-001 | Form: SWAB
Manufacturer: ProStock LLC
Category: otc | Type: HUMAN OTC DRUG LABEL
Date: 20200424

ACTIVE INGREDIENTS: BENZALKONIUM CHLORIDE 1.3 mg/1 mL
INACTIVE INGREDIENTS: WATER; GLYCERIN; PHENOXYETHANOL; BENZOIC ACID; POLYSORBATE 20; ALOE VERA LEAF; SODIUM CITRATE

Antibacterial Wet Wipes

Active Ingredient

Benzalkonium Chloride (0.13%)

Purpose

Antiseptic

Uses

For hand-washing to decrease bacteria on skin

Warnings

Flammable. Keep away from heat and flame.

For External use only.

Do not use

in eyes. In case of contact, rinse thoroughly with water.

Stop use & ask doctor

if rash/redness or irritation appears/develops and persist for more than 72 hours.

Keep out of reach from children

except under adult supervision. If swallowed, get medical help or contact a Poison Control Center

Directions

- Slowly peel back label and use one wipe. Reseal, keep closed to prevent evaporation.
- Thoroughly wipe hands, allow to dry out rinsing.
- Discard after single use

Inactive Ingredients

- Do not flush down toilet.
- Keep away from sunlight. Store at room temperature 20°-25°Celsius (68°-77° Fahrenheit)
- May discolor certain fabrics

Inactive Ingredients

Aqua, Glycerin, Phenoxyethanol, Benzoic Acid, Polysorbate 20, Aloe Barbadensis Leaf Juice, Sodium Citrate